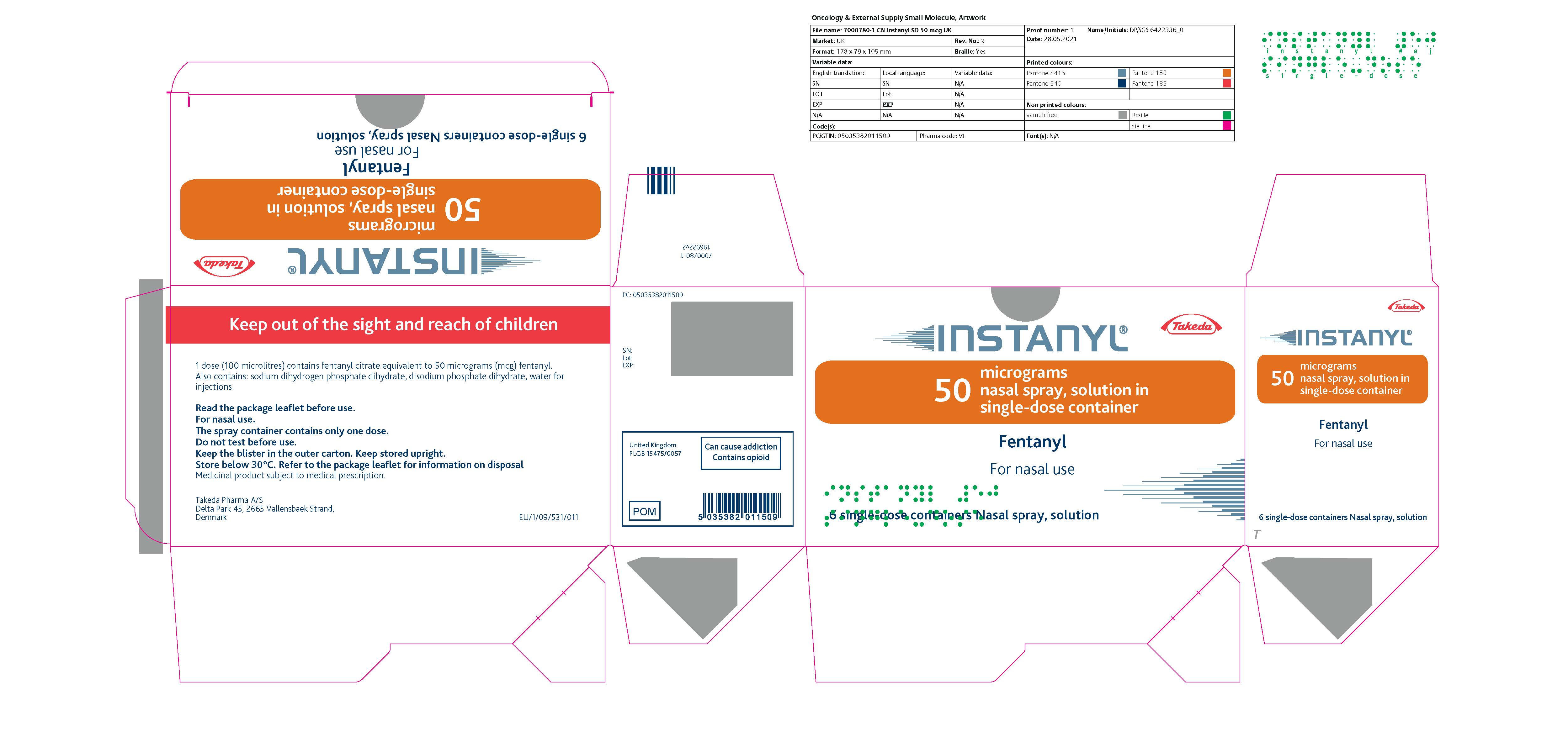 DRUG LABEL: Instanyl
NDC: 49396-0512 | Form: SPRAY
Manufacturer: Renaissance Lakewood LLC
Category: prescription | Type: HUMAN PRESCRIPTION DRUG LABEL
Date: 20241127
DEA Schedule: CII

ACTIVE INGREDIENTS: FENTANYL CITRATE 2 mg/1 mL
INACTIVE INGREDIENTS: WATER; SODIUM PHOSPHATE, DIBASIC; SODIUM PHOSPHATE, MONOBASIC

Instanyl Fentanyl Nasal Spray